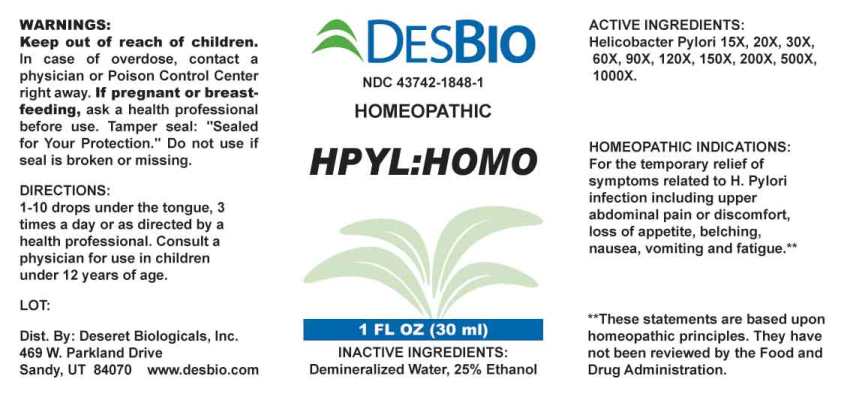 DRUG LABEL: HPYL HOMO
NDC: 43742-1848 | Form: LIQUID
Manufacturer: Deseret Biologicals, Inc.
Category: homeopathic | Type: HUMAN OTC DRUG LABEL
Date: 20240208

ACTIVE INGREDIENTS: HELICOBACTER PYLORI 15 [hp_X]/1 mL
INACTIVE INGREDIENTS: WATER; ALCOHOL

Drug Facts:

ACTIVE INGREDIENT:

Helicobacter Pylori 15X, 20X, 30X, 60X, 90X, 120X, 150X, 200X, 500X, 1000X.

HOMEOPATHIC INDICATIONS:

For the temporary relief of symptoms related to H. Pylori infection including upper abdominal pain or discomfort, loss of appetite, belching, nausea, vomiting and fatigue.**

**These statements are based upon homeopathic principles. They have not been reviewed by the Food and Drug Administration.

WARNINGS:

Keep out of reach of children. In case of overdose, contact a physician or Poison Control Center right away.

If pregnant or breast-feeding, ask a health professional before use.

Tamper seal: "Sealed for Your Protection." Do not use if seal is broken or missing.

Keep out of reach of children. In case of overdose, contact a physician or Poison Control Center right away.

DIRECTIONS:

1-10 drops under the tongue, 3 times a day or as directed by a health professional. Consult a physician for use in children under 12 years of age.

HOMEOPATHIC INDICATIONS:

For the temporary relief of symptoms related to H. Pylori infection including upper abdominal pain or discomfort, loss of appetite, belching, nausea, vomiting and fatigue.**

**These statements are based upon homeopathic principles. They have not been reviewed by the Food and Drug Administration.

INACTIVE INGREDIENTS:

Demineralized Water, 25% Ethanol

QUESTIONS:

Dist. By: Deseret Biologicals, Inc.
469 W. Parkland Drive
Sandy, UT 84070 www.desbio.com

PACKAGE LABEL DISPLAY:

DESBIO

NDC 43742-1848-1

HOMEOPATHIC

HPYL:HOMO

1 FL OZ (30 ml)